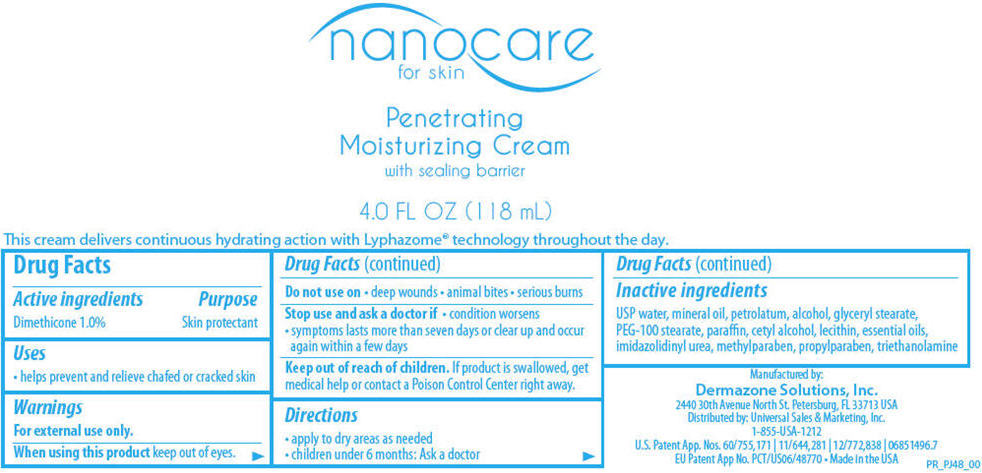 DRUG LABEL: nanocare
NDC: 58466-024 | Form: CREAM
Manufacturer: Deramzone Solutions, Inc.
Category: otc | Type: HUMAN OTC DRUG LABEL
Date: 20121018

ACTIVE INGREDIENTS: Dimethicone 10 mg/1 mL
INACTIVE INGREDIENTS: water; mineral oil; petrolatum; alcohol; glyceryl monostearate; PEG-100 stearate; paraffin; cetyl alcohol; imidurea; methylparaben; propylparaben; trolamine

nanocare for skin
Penetrating Moisturizing Cream

Drug Facts

Active ingredients

Dimethicone 1.0%

Purpose

Skin protectant

Uses

- helps prevent and relieve chafed or cracked skin

Warnings

For external use only.

When using this product keep out of eyes.

Do not use on

- deep wounds
- animal bites
- serious burns

Stop use and ask a doctor if

- condition worsens
- symptoms lasts more than seven days or clear up and occur again within a few days

Keep out of reach of children. If product is swallowed, get medical help or contact a Poison Control Center right away.

Directions

- apply to dry areas as needed
- children under 6 months: Ask a doctor

Inactive ingredients

USP water, mineral oil, petrolatum, alcohol, glyceryl stearate, PEG-100 stearate, paraffin, cetyl alcohol, lecithin, essential oils, imidazolidinyl urea, methylparaben, propylparaben, triethanolamine

Manufactured by:
Dermazone Solutions, Inc.
2440 30th Avenue North St. Petersburg, FL 33713 USA

Distributed by: Universal Sales & Marketing, Inc.

PRINCIPAL DISPLAY PANEL - 118 mL Jar Label

nanocare
for skin

Penetrating
Moisturizing Cream
with sealing barrier

4.0 FL OZ (118 mL)